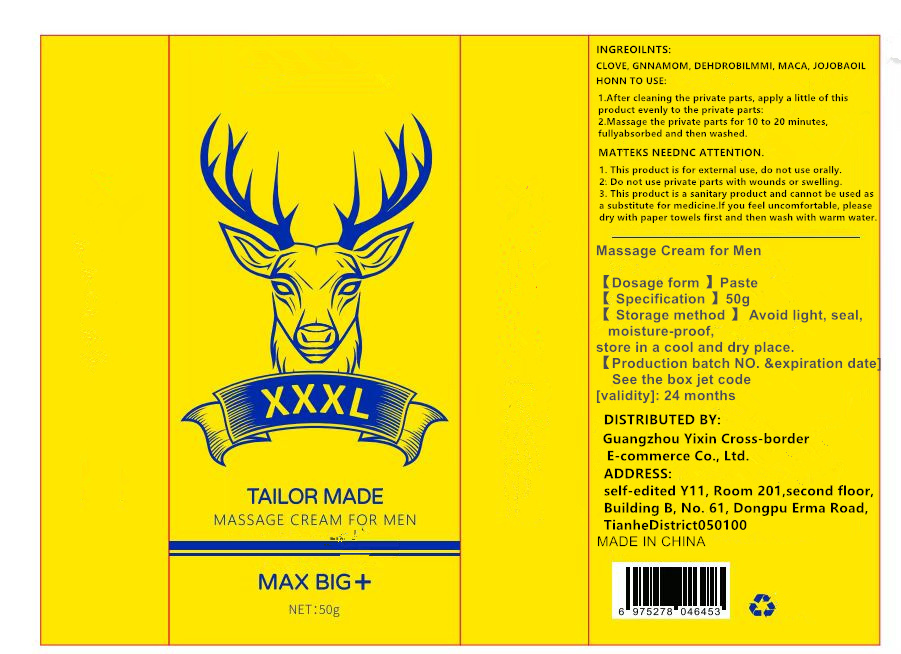 DRUG LABEL: men massage cream
NDC: 84778-003 | Form: EMULSION
Manufacturer: Guangzhou Yixin Cross-border E-commerce Co., Ltd.
Category: otc | Type: HUMAN OTC DRUG LABEL
Date: 20240927

ACTIVE INGREDIENTS: ASIAN GINSENG 2 g/100 g
INACTIVE INGREDIENTS: CLOVE; DENDROBIUM DENSIFLORUM WHOLE; JOJOBA OIL; MACAMIDE 2; CINNAMON

COMPONENTS

ginseng 2%

PURPOSE

Private care treatment for men

INDICATIONS AND USAGE

1. After cleaning the private parts, apply a little of this product evenly to the private parts;

2. Massage the private parts for 10 to 20 minutes, fully absorbed and then washed.

WARNINGS

1. This product is for external use, do not use orally;

2. Do not use private parts with wounds or swelling.

3. This product is a sanitary product, not a substitute for medicine. Please use it first if you feel uncomfortable

Dry with paper towels and rinse with warm water.

DOSAGE AND ADMINISTRATION

For external use only.

Do not use if there are wounds on the skin.

If there is discomfort during use, such as burning, pain, tightness, itching and other symptoms,

Please dry with paper towels and rinse with warm water.

WHEN USING

do not apply on other parts of the body

avoid contact with the eyes. in case of accidental contact, rinse eyes with large amounts of cool tap water.

STOP USE

on broken or irritated skin

KEEP OUT OF REACH OF CHILDREN

If sxralowed, get medical help or contact a Poison Conirol Cenler ngiht away.

INACTIVE INGREDIENT

ginseng, cloves, cinnamon, Dendrobium, maca, Jojoba oil